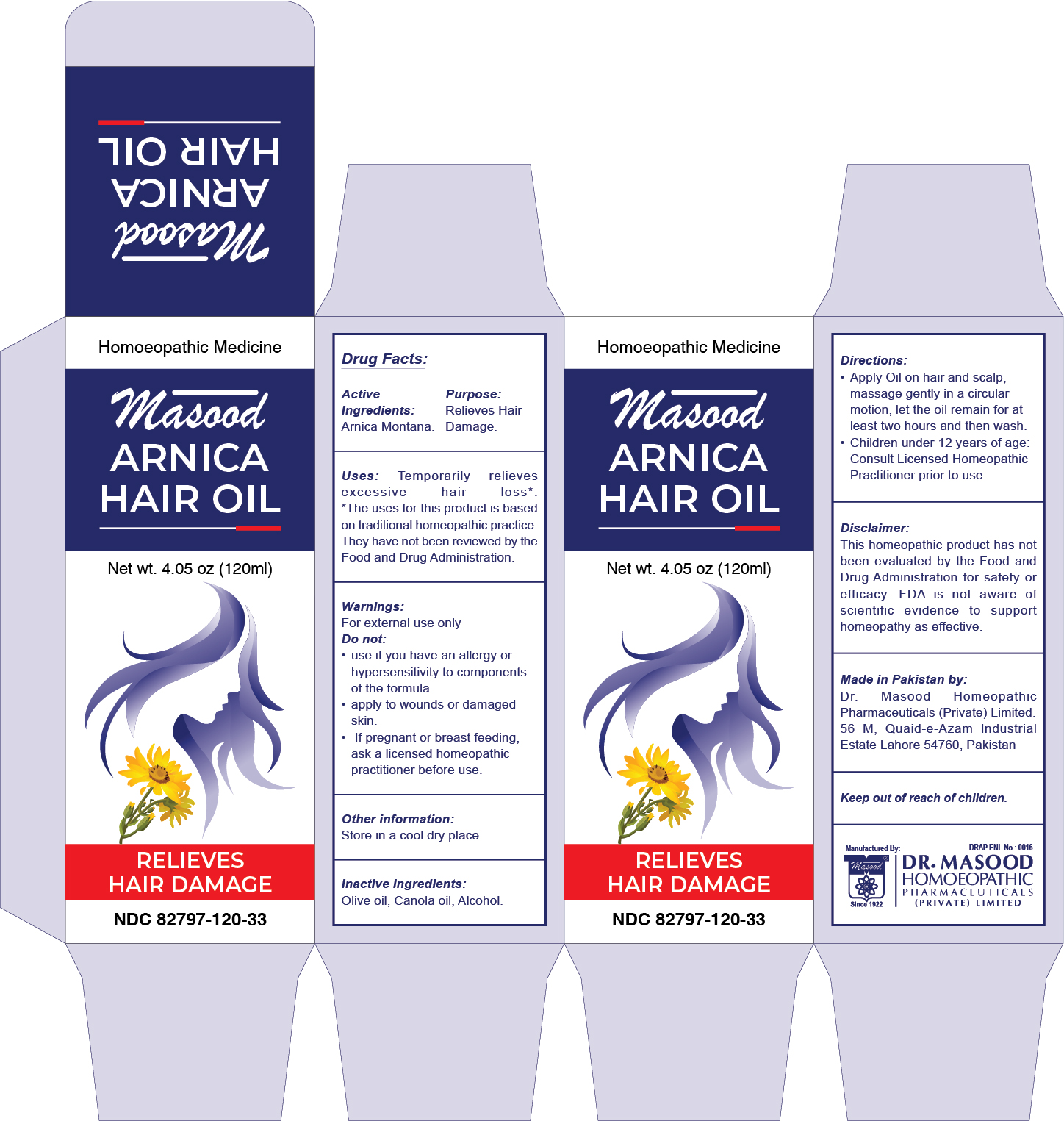 DRUG LABEL: Masood Arnica Hair Oil
NDC: 82797-120 | Form: OIL
Manufacturer: Dr. Masood Homeopathic Pharmaceuticals Private Limited
Category: homeopathic | Type: HUMAN OTC DRUG LABEL
Date: 20240109

ACTIVE INGREDIENTS: ARNICA MONTANA FLOWER 12 g/120 mL
INACTIVE INGREDIENTS: OLIVE OIL 75 mL/120 mL; ALCOHOL 11 mL/120 mL; CANOLA OIL 34 mL/120 mL

Masood Arnica Hair Oil

Directions:

- Apply Oil on hair and scalp, massage gently in a circular motion, let the oil remain for at least two hours and then wash
- Children under 12 years of age: Consult Licensed Homeopathic Practitioner prior to use.

Active Ingredients

Arnica Montana

Purpose

Relieves Hair Damage

Keep out of reach of children.

Inactive ingredients:

Olive oil, Canola oil, Alcohol

Uses:

Temporarily relieves excessive hair loss. *

*The uses for this product is based on traditional homeopathic practice. They have not been reviewed by the Food and Drug Administration.

Warnings:

For external use only

Do not:

- use if you have an allergy or hypersensitivity to components of the formula
- apply to wounds or damaged skin
- If pregnant or breast feeding, ask a licensed homeopathic practitioner before use.